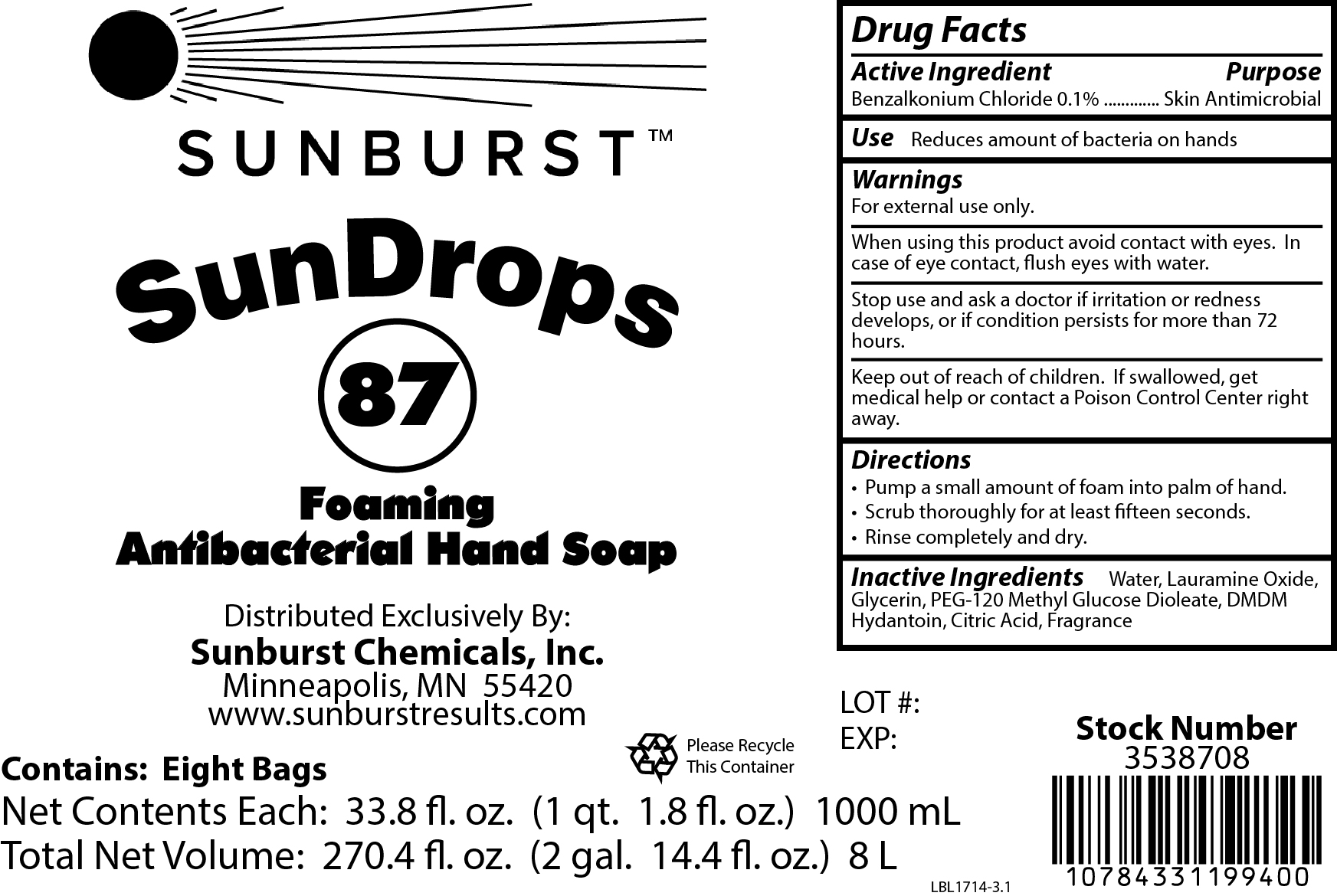 DRUG LABEL: SunDrops 87
NDC: 63621-387 | Form: SOAP
Manufacturer: Sunburst Chemicals, Inc.
Category: otc | Type: HUMAN OTC DRUG LABEL
Date: 20251111

ACTIVE INGREDIENTS: BENZALKONIUM CHLORIDE 1 mg/1 mL
INACTIVE INGREDIENTS: CITRIC ACID MONOHYDRATE; WATER; GLYCERIN; LAURAMINE OXIDE; PEG-120 METHYL GLUCOSE DIOLEATE; DMDM HYDANTOIN

SunDrops 87

Active Ingredient

Benzalkonium Chloride 0.1%

Purpose

Skin Antimicrobial

Use

Reduces amount of bacteria on hands

Warnings

For external use only.

When using this product avoid contact with eyes. In case of eye contact, flush eyes with water.

Stop use and ask a doctor if irritation or redness develops, or if condition persists for more than 72 hours.

Keep out of reach of children. If swallowed, get medical help or contact a Poison Control Center right away.

Directions

- Pump a small amount of foam into palm of hand.
- Scrub thoroughly for at least fifteen seconds.
- Rinse completely and dry.

Inactive Ingredients

Water, Lauramine Oxide, Glycerin, PEG-120 Methyl Glycose Dioleate, DMDM Hydantoin, Citric Acid, Fragrance